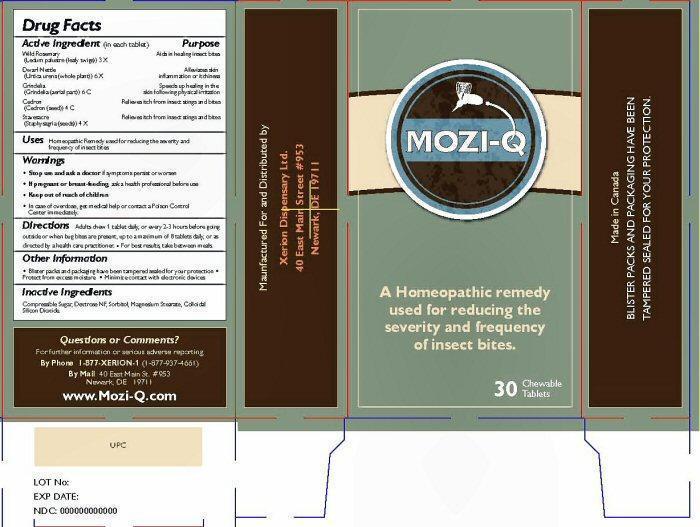 DRUG LABEL: MOZI-Q
NDC: 53590-100 | Form: TABLET, CHEWABLE
Manufacturer: Xerion Dispensary Ltd.
Category: homeopathic | Type: HUMAN OTC DRUG LABEL
Date: 20251216

ACTIVE INGREDIENTS: LEDUM PALUSTRE TWIG 3 [hp_X]/1 1; URTICA URENS 6 [hp_X]/1 1; SIMABA CEDRON SEED 4 [hp_C]/1 1; DELPHINIUM STAPHISAGRIA SEED 4 [hp_X]/1 1; GRINDELIA HIRSUTULA FLOWERING TOP 6 [hp_C]/1 1
INACTIVE INGREDIENTS: SUCROSE; DEXTROSE; SORBITOL; MAGNESIUM STEARATE; SILICON DIOXIDE

Active Ingredient (in each tablet)

Wild Rosemary (Ledum palustre (leafy twigs)) 3 X

Dwarf Nettle (Urtica urens (whole plant)) 6 X

Grindelia (Grindelia (aerial part)) 6 C

Cedron (Cedron (seed)) 4 C

Stavesacre (Staphysagria (seeds)) 4 X

Purpose

Aids in healing insect bites

Alleviates skin inflammation or itchiness

Speeds up healing in the skin following physical irritation

Relieves itch from insect stings and bites

Relieves itch from insect stings and bites

Uses

Homeopathic Remedy used for reducing the severity and frequency of insect bites.

Warnings

Stop use and ask a doctor if symptoms persist or worsen

If pregnant or breast-feeding, ask a health professional before use

Keep out of reach of children

In case of overdose, get medical help or contact a Poison Control immediately.

Directions

Adults chew 1 tablet daily, or every 2-3 hours before going outside or when bug bites are present, up to a maximum of 8 tablets daily, or as directed by a health care practitioner. For best results, take between meals.

Other Information

Blister packs and packaging have been tampered sealed for your protection. Protect from excess moisture. Minimize contact with electronic devices.

Questions or Comments?

By Phone 1-877-XERION-1 (1-877-937-4661)

By Mail 1077 Pacific Coast Hws #307

Seal Beach, CA 90740

Learn More Online at www.Mozi-QAmerica.com

Inactive Ingredients

Compressible Sugar, Dextrose NF, Sorbitol, Magnesium Stearate, Colloidal Silicon Dioxide.

MOZI-Q

Homeopathic remedy used for reducing the severity of insect bites

Relieves redness, swelling and itch from bug bites.

30 Chewable tablets

Distributed by

Xerion Dispensary Ltd.

150, 4625 Varsity Drive NW

Calgary, Alberta, Canada T3A 0Z9

Manufactured by Herba Sante

For futher information or serious adverse reporting

By Phone 1-877-XERION-1 ((1-877-937-4661)

By Mail1077 Pacific Coast Hws #307 Seal Beach, CA 90740

BLISTER PACKS AND PACKAGING HAVE BEEN TAMPERED SEALED FOR YOUR PROTECTION.

Made in Canada

Keep out of reach of children.

PACKAGE LABEL

res